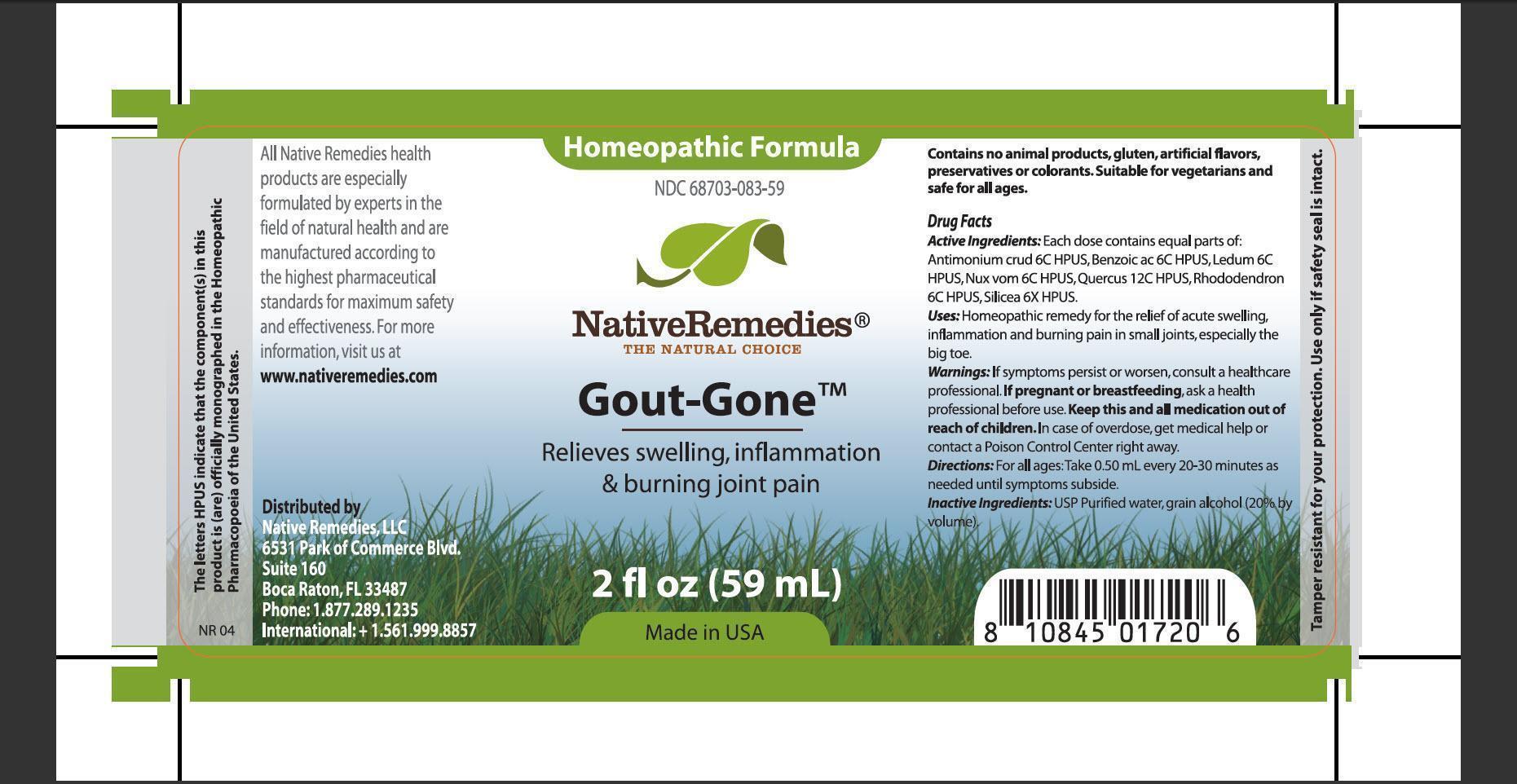 DRUG LABEL: Gout Gone
NDC: 68703-083 | Form: TINCTURE
Manufacturer: Native Remedies, LLC
Category: homeopathic | Type: HUMAN OTC DRUG LABEL
Date: 20130415

ACTIVE INGREDIENTS: ANTIMONY TRISULFIDE 6 [hp_C]/1 mL; BENZOIC ACID 6 [hp_C]/1 mL; LEDUM PALUSTRE TWIG 6 [hp_C]/1 mL; STRYCHNOS NUX-VOMICA SEED 6 [hp_C]/1 mL; QUERCUS ROBUR NUT 12 [hp_C]/1 mL; RHODODENDRON AUREUM LEAF 6 [hp_C]/1 mL; SILICON DIOXIDE 6 [hp_X]/1 mL
INACTIVE INGREDIENTS: WATER; ALCOHOL

Gout Gone

PURPOSE

Relieves swelling, inflammation and burning joint pain

ACTIVE INGREDIENT

Active Ingredients: Antimonium crud 6C HPUS, Benzoic ac 6C HPUS, Ledum 6C HPUS, Nux vom 6C HPUS, Quercus 12C HPUS, Rhododendron 6C HPUS, Silicea 6X HPUS

INDICATIONS AND USAGE

Uses: Homeopathic remedy for the relief of acute swelling, inflammation and burning pain in small joint, especially the big toe

WARNINGS

Warnings: If symptoms persist or worsen, consult a healthcare professional

PREGNANCY OR BREAST FEEDING

If pregnant or breastfeeding, ask a health professional before use

KEEP OUT OF REACH OF CHILDREN

Keep this and all medication out of reach of children

OVERDOSAGE

In case of overdose, get medical help or contact a Poison Control Center right away

DOSAGE AND ADMINISTRATION

Directions: For all ages: Take 0.50 mL every 20-30 minutes as needed until symptoms subside

INACTIVE INGREDIENT

Inactive Ingredients: USP Purified water, grain alcohol (20% by volume)

PATIENT COUNSELING INFORMATION

The letters HPUS indicate that the component(s) in this product is (are) officially monographed in the Homeopathic Pharmacopoeia of the United States

All Native Remedies health products are especially formulated by experts in the field of natural health and are manufactured according to the highest pharmaceutical standards for maximum safety and effectiveness. For more information, visit us at www.nativeremedies.com

Distributed by
Native Remedies, LLC
6531 Park of Commerce Blvd.
Suite 160
Boca Raton, FL 33487
Phone:1.877.289.1235
International:+1.561.999.8857

Contains no animal products, artificial flavors, preservatives or colorants. Suitable for vegetarians and safe for all ages

STORAGE AND HANDLING

Tamper resist for your protection. Use only if safety seal is intact